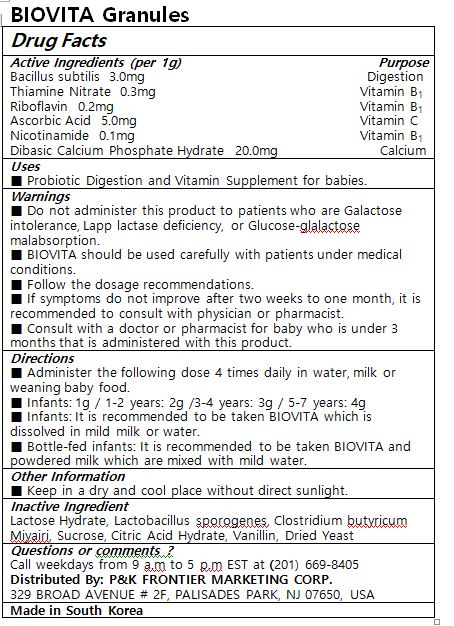 DRUG LABEL: BIOVITA
NDC: 72689-0032 | Form: GRANULE
Manufacturer: OASIS TRADING
Category: otc | Type: HUMAN OTC DRUG LABEL
Date: 20190114

ACTIVE INGREDIENTS: BACILLUS SUBTILIS 3 mg/1 g; CALCIUM PHOSPHATE, DIBASIC, DIHYDRATE 20 mg/1 g; THIAMINE MONONITRATE 0.3 mg/1 g; RIBOFLAVIN 0.2 mg/1 g; ASCORBIC ACID 5 mg/1 g; NIACINAMIDE 0.1 mg/1 g
INACTIVE INGREDIENTS: LACTOSE MONOHYDRATE; SUCROSE; CITRIC ACID MONOHYDRATE; VANILLIN; YEAST, UNSPECIFIED; BACILLUS COAGULANS

Active ingredients (1g contains)
Bacillus subtilis 3.0 mg
Thiamine Nitrate 0.3 mg
Riboflavin 0.2 mg
Ascorbic Acid 5.0 mg
Nicotinamide 0.1 mg
Dibasic Calcium Phosphate Hydrate 20.0 mg

PURPOSE

Digestion, Vitamins, and Calcium

INDICATIONS AND USAGE

Probiotic Digestion and Vitamin Supplement for babies.

DOSAGE AND ADMINISTRATION

Administer the following dose 4 times daily in water, milk or weaning baby food.
Infants: 1g / 1-2 years: 2g /3-4 years: 3g / 5-7 years: 4g
Infants: It is recommended to be taken BIOVITA which is dissolved in mild milk or water.
Bottle-fed infants: It is recommended to be taken BIOVITA and powdered milk which are mixed with mild water.

WARNINGS

Do not administer this product to patients who are Galactose intolerance, Lapp lactase deficiency, or Glucose-glalactose malabsorption.

BIOVITA should be used carefully with patients under medical conditions.

Follow the dosage recommendations.

If symptoms do not improve after two weeks to one month, it is recommended to consult with physician or pharmacist.

Consult with a doctor or pharmacist for baby who is under 3 months that is administered with this product.

Keep in a dry and cool place without direct sunlight.

Keep out of reach of the children.

INACTIVE INGREDIENT

Lactose Hydrate, Lactobacillus sporogenes, Clostridium butyricum Miyairi, Sucrose, Citric Acid Hydrate, Vanillin, Dried Yeast